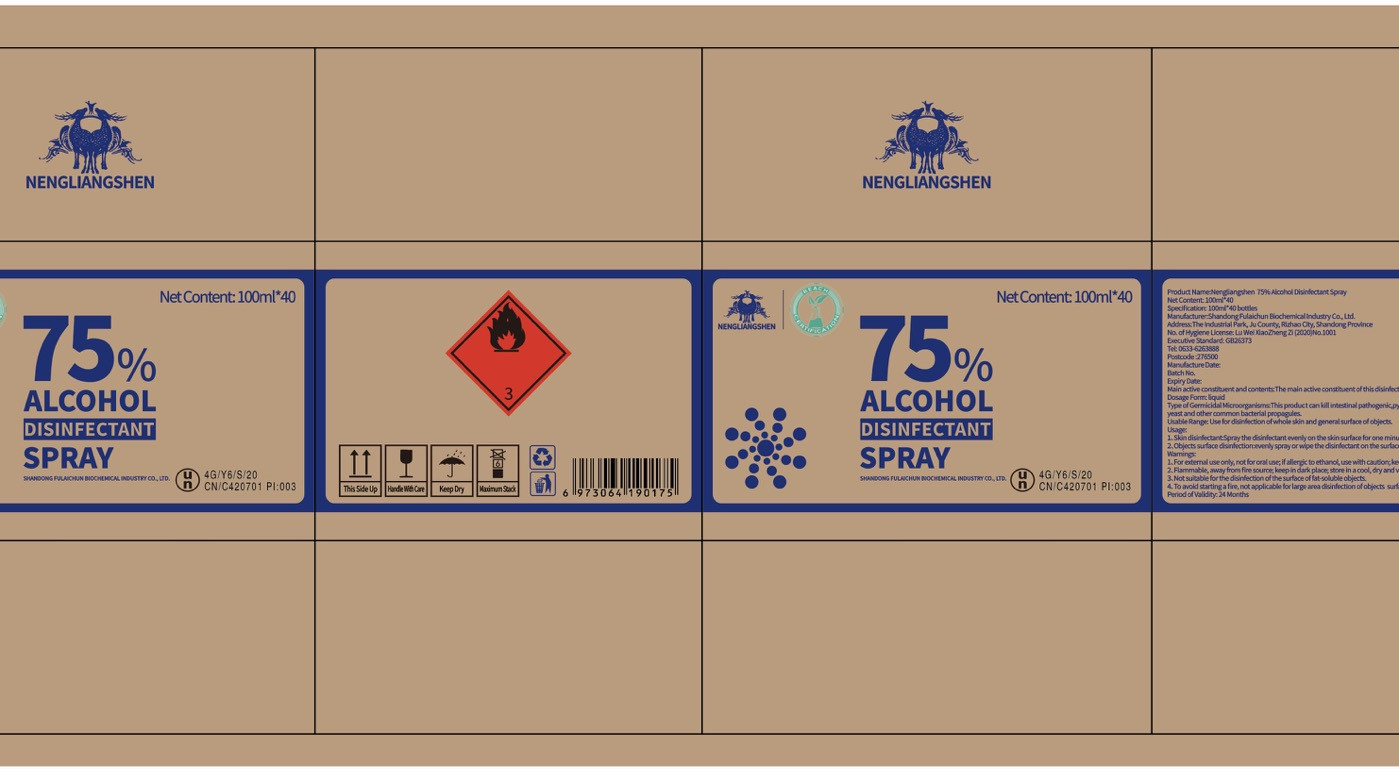 DRUG LABEL: ALCOHOL DISINFECTANTSPRAY
NDC: 54522-001 | Form: LIQUID
Manufacturer: Shandong Fulaichun Biochemical Industry Co., Ltd
Category: otc | Type: HUMAN OTC DRUG LABEL
Date: 20200515

ACTIVE INGREDIENTS: ALCOHOL 75 mL/100 mL
INACTIVE INGREDIENTS: WATER

DOSAGE AND ADMINISTRATION

store in a cool, dry and ventilated place.

INACTIVE INGREDIENT

water

INDICATIONS AND USAGE

1.Skin disinfectant:Spray the disinfectant evenly on the skin surface for one minute.

2.objects surface disinfection:evenly Spray or wipe the disinfectant on the Surface of the objects for three minutes.

ACTIVE INGREDIENT

ALCOHOL

keep out of reach of children

PURPOSE

Disinfection
Sterilization

WARNINGS

1.For external use only, not for oral use; if alergic to ethanol, use with caution; keep out of reach of children.

2.Flammable, away from fire source; keep in dark place; store in a cool, dry and ventilated place.
3.Not suitable for the disinfection of the surface of fat-soluble objects.
4.To avoid starting a fire, not applicable for large area disinfection of objects surface.